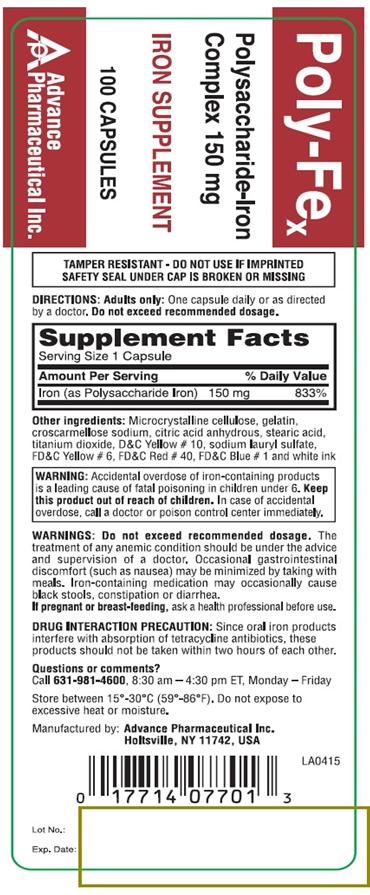 DRUG LABEL: Polysaccharide-Iron
NDC: 17714-077 | Form: CAPSULE
Manufacturer: Advance Pharmaceutical Inc.
Category: otc | Type: HUMAN OTC DRUG LABEL
Date: 20191223

ACTIVE INGREDIENTS: IRON 150 mg/1 1
INACTIVE INGREDIENTS: CELLULOSE, MICROCRYSTALLINE; GELATIN; CROSCARMELLOSE SODIUM; CITRIC ACID MONOHYDRATE; STEARIC ACID; TITANIUM DIOXIDE; D&C YELLOW NO. 10; SODIUM LAURYL SULFATE; FD&C YELLOW NO. 6; FD&C RED NO. 40; FD&C BLUE NO. 1

Polysaccharide-Iron Complex 150 mg

Drug Facts

.

Active Ingredient

(in each capsule)

Iron (as Polysaccharide Iron) 150 mg

Purpose

Iron Supplement

Uses

- Iron Supplement

WARNINGS

Do not exceed recommended dosage. The treatment of any anemic condition should be under the advice and supervision of a doctor. Occasional gastrointestinal discomfort (such as nausea) may be minimized by taking with meals. Iron-containing medication may occasionally cause black stools, constipation or diarrhea. If pregnant or breast feeding, ask a health professional before use.

Accidental overdose of Iron containing products is a leading cause of fatal poisoning in children under 6.

DRUG INTERACTION PRECAUSION: Since oral iron products interfere with absorption of tetracycline antibiotics, these products should not be taken within two hours of each other.

Keep out of reach of children.

In case of accidental overdose, call a doctor or poison control center immediately.

Directions

Adults only: One capsule daily or as directed by a doctor. Do not exceed recommended dosage.

Other Information

- store at 15-30 °C (59-86 °F). Do not expose to excessive heat or moisture.

Inactive Ingredients

Microcrystalline Cellulose, geltain, corscarmellose sodium, citric acid anhydrous, stearic acid, titanium dioxide, D&C Yellow #10, sodium lauryl sulfate, FD&C Yellow #6, FD&C Red#40, FD&C Blue #1and white ink

Questions or Comments

TAMPER RESISTENT: DO NOT USE IF IMPRINTED SAFETY SEAL UNDER CAP IS BROKEN OR MISSING

PACKAGE LABEL.PRINCIPAL DISPLAY PANEL

NDC